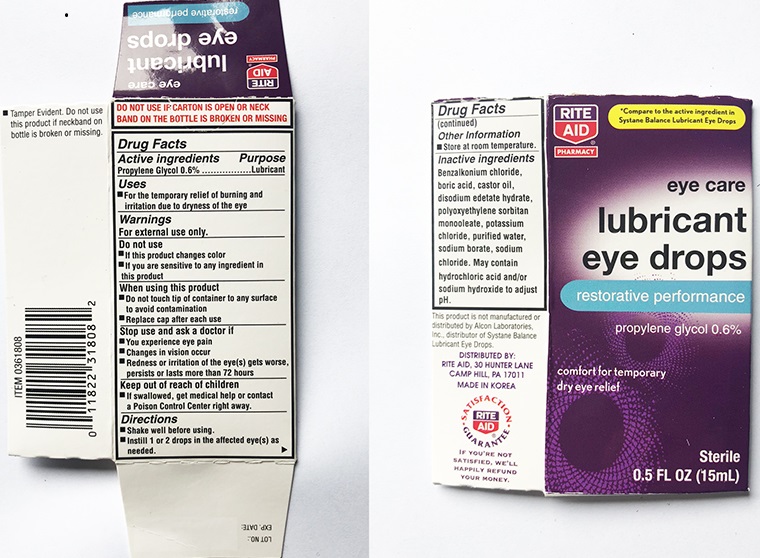 DRUG LABEL: Rite Aid Lubricant Eye Drops Restorative Performance
NDC: 11822-3728 | Form: SOLUTION/ DROPS
Manufacturer: Rite Aid Corporation
Category: otc | Type: HUMAN OTC DRUG LABEL
Date: 20231220

ACTIVE INGREDIENTS: PROPYLENE GLYCOL 0.6 g/100 mL
INACTIVE INGREDIENTS: BENZALKONIUM CHLORIDE; BORIC ACID; CASTOR OIL; EDETATE DISODIUM; PEG-6 SORBITAN OLEATE; POTASSIUM CHLORIDE; WATER; SODIUM BORATE; SODIUM CHLORIDE; HYDROCHLORIC ACID; SODIUM HYDROXIDE

Rite Aid Lubricant Eye Drops Restorative Performance 15 mL (PLD)

Active ingredients

Propylene glycol....0.6%

Purpose

Propylene glycol............ Lubricant

Uses
• for the temporary relief of burning and irritation due to dryness of the eye

Warnings
For external use only

Do not use
• if this product changes color
• if you are sensitive to any ingredient in this product

When using this product
• do not touch the tip of container to any surface to avoid contamination
• replace cap after each use

Stop use and ask a doctor if
• you experience eye pain
• changes in vision occur
• redness or irritation of the eye(s) gets worse, persists or lasts more than 72 hours

Keep out of reach of children
If swallowed, get medical help or contact a Poison Control Center right away.

Directions

- Shake well before using.
- Instill 1 or 2 drops in the affected eye(s) as needed

Other information

- Store at room temperature.

Inactive ingredients

Benzalkonium chloride, boric acid, castor oil, disodium edetate hydrate, polyoxyethylene sorbitan monooleate, potassium chloride, purified water, sodium borate, sodium chloride. May contain hydrochloric acid and/or sodium hydroxide to adjust pH.